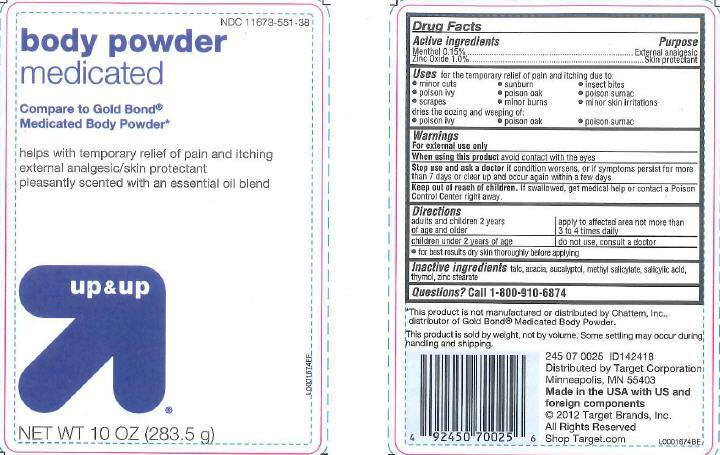 DRUG LABEL: Medicated
NDC: 11673-551 | Form: POWDER
Manufacturer: Target Corporation
Category: otc | Type: HUMAN OTC DRUG LABEL
Date: 20130121

ACTIVE INGREDIENTS: MENTHOL 1.5 mg/1 g; ZINC OXIDE 10 mg/1 g
INACTIVE INGREDIENTS: TALC; ACACIA; EUCALYPTOL; METHYL SALICYLATE; SALICYLIC ACID; THYMOL; ZINC STEARATE

Drug Facts

Active Ingredients

Menthol 0.15%

Zinc oxide 1.0%

Purpose

External analgesic

Skin protectant

Uses

Uses for the temporary relief of paina and itching due to:

- monor cuts
- sunburn
- insect bites
- poison ivy
- poison oak
- poison sumac
- scrapes
- minor burns
- minor skin irritations

dries the oozing and weeping of:

- poison ivy
- poison oak
- poison sumac

Warnings

For external use only

When using

When using this product avoid contact with the eyes

Stop use

Stop use and ask a doctor if conditin worsens, or if symptoms persist for more than 7 days or clear up and occur again within a few days

Keep out of reach of children. If swallowed, get medical help or contact a Poison Control Center right away

Directions

adults and children 2 years of age and older - apply to affected area not more than 3 to 4 times daily

children under 2 years of age - do not use, consult a doctor

- for best results dry skin thoroughly before applying

Inactive ingredients

Inactive ingredients talc, acacia, eucalyptol, methyl salicylate, salicylic acid, thymol, zinc stearate

Questions

Questions? Call 1-800-910-6874

disclaimer

This product is not manufactured or distributed by Chattem, Inc., distributor of Gold Bond Medicated Body Powder.

This product is sold by weight, not by volume. Some settling may occur during handling and shipping

Made in the USA with US and foreign components

Adverse Reactions

Distributed by Target Corporation

Minneapolis, MN 55403

Shop Target.com

Principal display panel

NDC 11673-551-38

body powder

medicated

compare to Gold bond

Medicated Body Powder

helps with temporary relief of pain and itchng

external analgesic/skin protectant

pleasantly scented with an essential oil blend

up + up

NET WT 10 OZ (283.5 g)